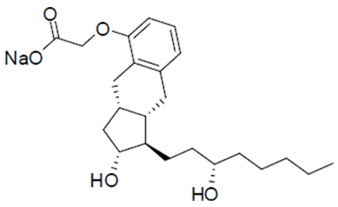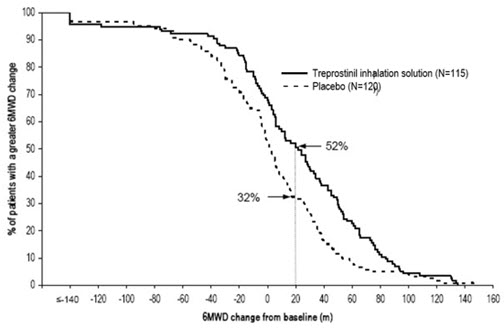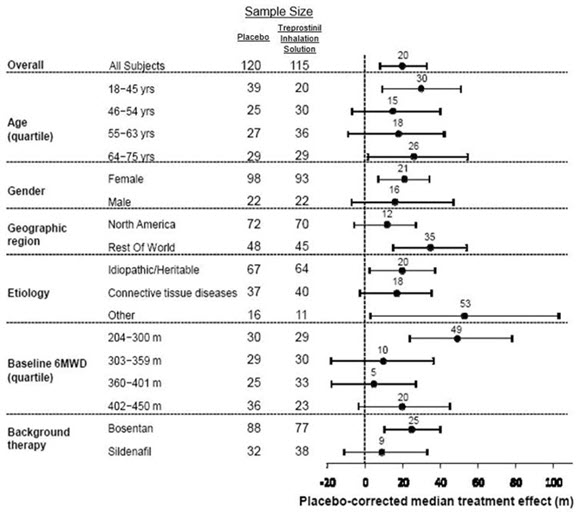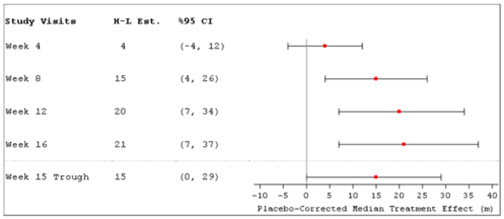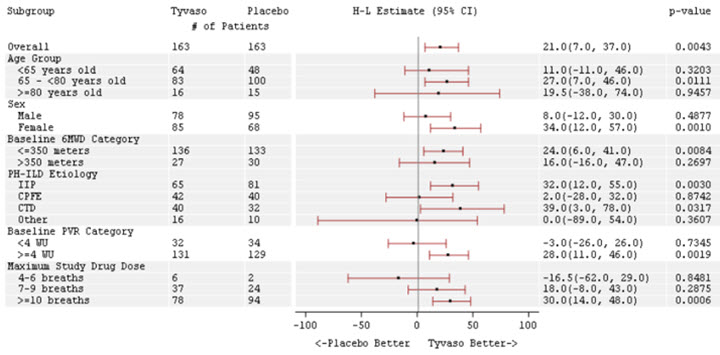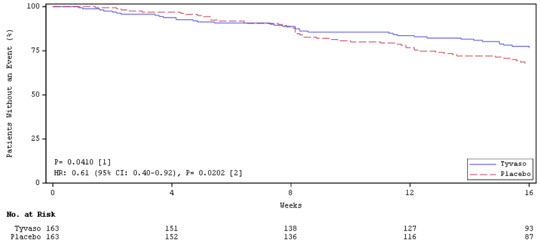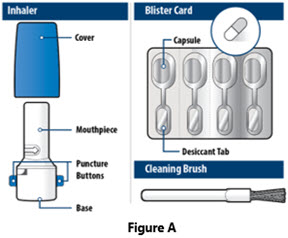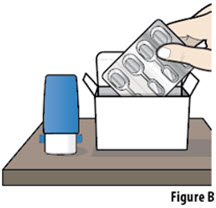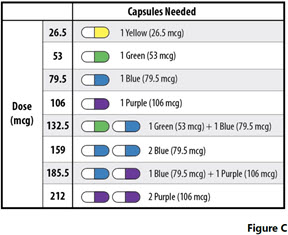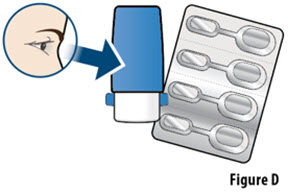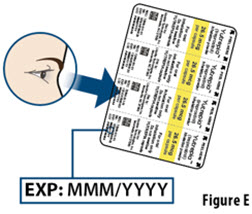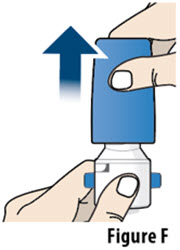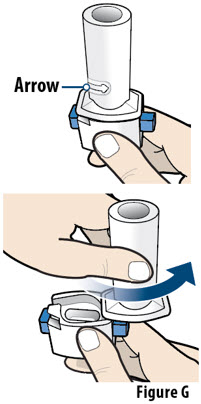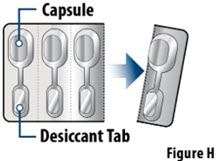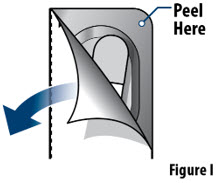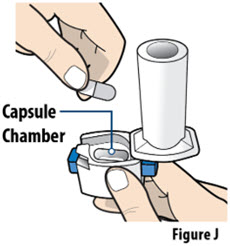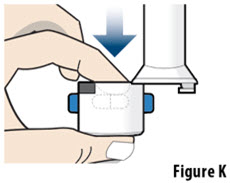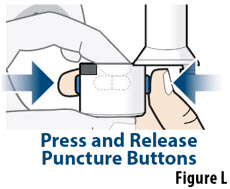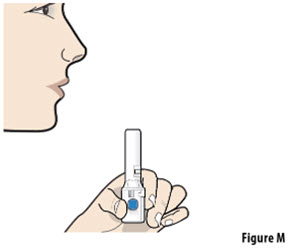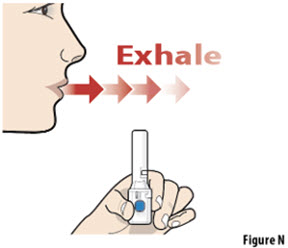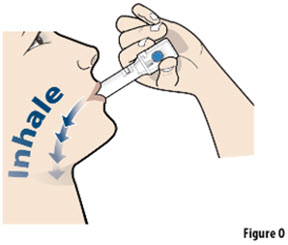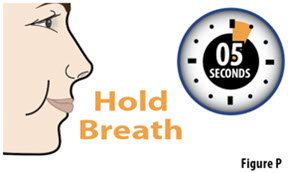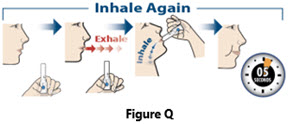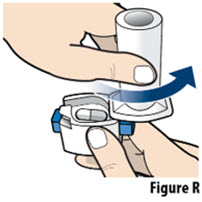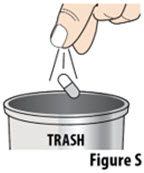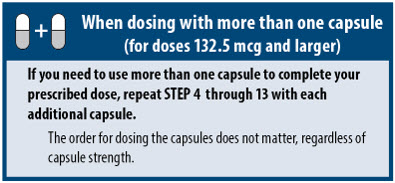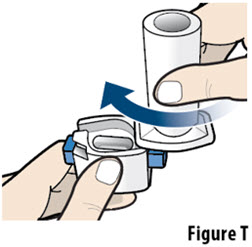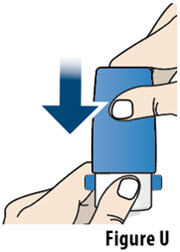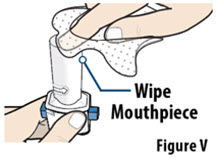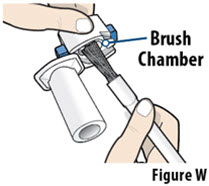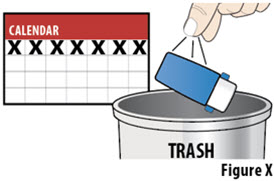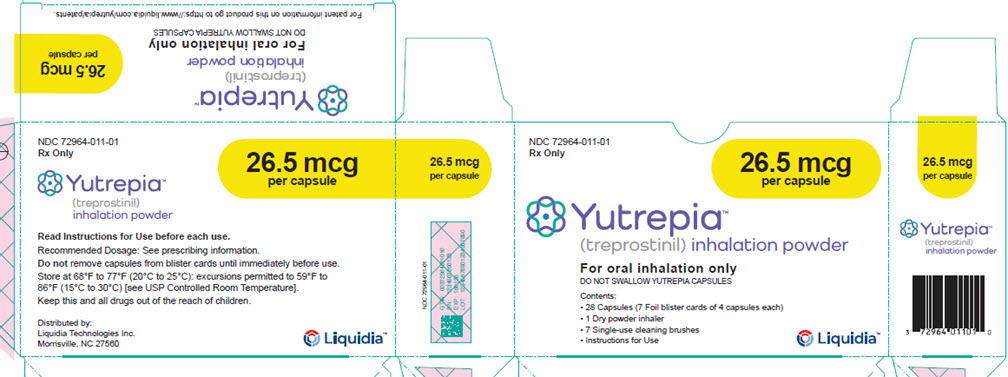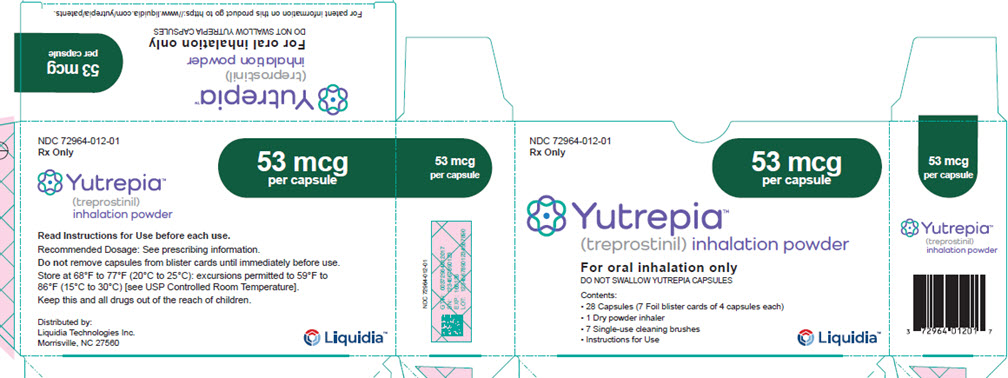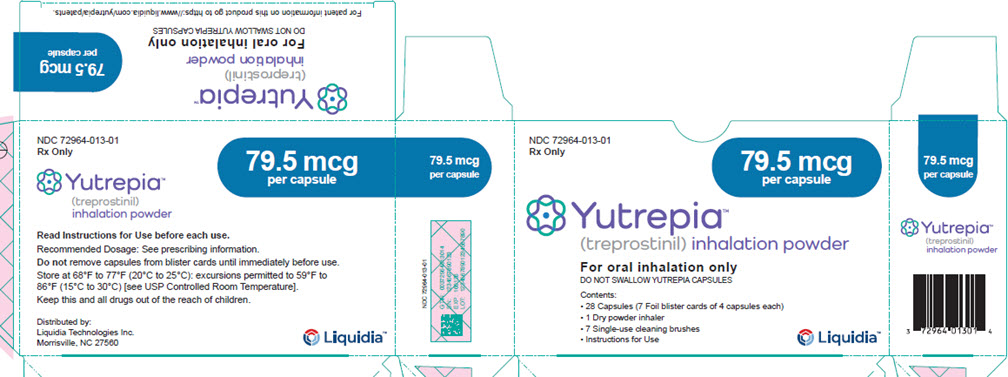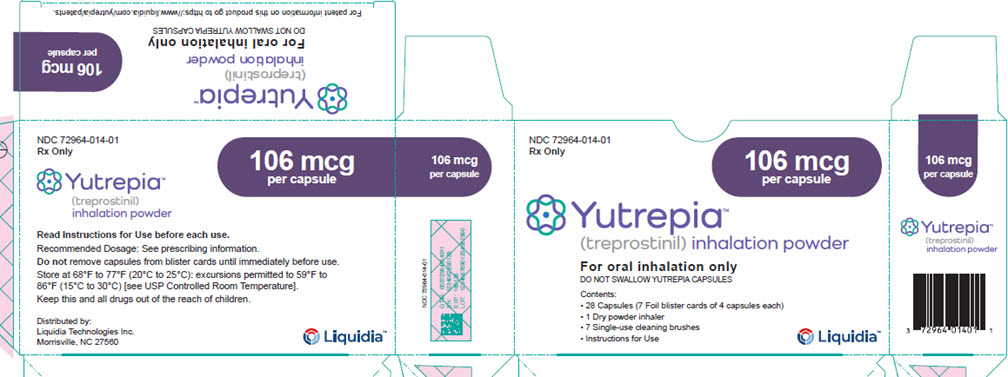 DRUG LABEL: Yutrepia
NDC: 72964-011 | Form: CAPSULE
Manufacturer: Liquidia Technologies, Inc.
Category: prescription | Type: HUMAN PRESCRIPTION DRUG LABEL
Date: 20250908

ACTIVE INGREDIENTS: TREPROSTINIL SODIUM 26.5 ug/1 1
INACTIVE INGREDIENTS: TREHALOSE DIHYDRATE; POLYSORBATE 80; LEUCINE; TRISODIUM CITRATE DIHYDRATE; SODIUM CHLORIDE

HIGHLIGHTS OF PRESCRIBING INFORMATION

These highlights do not include all the information needed to use YUTREPIA™ safely and effectively. See full prescribing information for YUTREPIA™.
YUTREPIA™ (treprostinil) inhalation powder, for oral inhalation
Initial U.S. Approval: 2002

1 INDICATIONS AND USAGE

- Pulmonary arterial hypertension (PAH; WHO Group 1) to improve exercise ability. Studies establishing effectiveness predominately included patients with NYHA Functional Class III symptoms and etiologies of idiopathic or heritable PAH (56%) or PAH associated with connective tissue diseases (33%). (1.1)
- Pulmonary hypertension associated with interstitial lung disease (PH-ILD; WHO Group 3) to improve exercise ability. The study establishing effectiveness predominately included patients with etiologies of idiopathic interstitial pneumonia (IIP) (45%) inclusive of idiopathic pulmonary fibrosis (IPF), combined pulmonary fibrosis and emphysema (CPFE) (25%), and WHO Group 3 connective tissue disease (22%). (1.2)

2 DOSAGE AND ADMINISTRATION

- For oral inhalation only. Do not swallow YUTREPIA capsules. Use only with the provided inhaler (2)
- YUTREPIA should be administered 3 to 5 times per day. The contents of each capsule can be inhaled in 2 breaths. (2.1)
- See Dosage and Administration for full instructions on dosing of patients who are treprostinil-naïve or transitioning from treprostinil inhalation solution to YUTREPIA (2.1)

3 DOSAGE FORMS AND STRENGTHS

YUTREPIA inhalation powder contained in capsule is available in 4 strengths: 26.5 mcg, 53 mcg, 79.5 mcg, 106 mcg (3)

4 CONTRAINDICATIONS

None (4)

5 WARNINGS AND PRECAUTIONS

- Treprostinil may cause symptomatic hypotension. (5.1)
- Treprostinil inhibits platelet aggregation and increases the risk of bleeding. (5.2)
- Dosage adjustments may be necessary if inhibitors or inducers of CYP2C8 are added or withdrawn. (5.3, 7.1)
- May cause bronchospasm: Patients with a history of hyperreactive airway disease may be more sensitive. (5.4)

6 ADVERSE REACTIONS

Most common adverse reactions with YUTREPIA (³10%) are cough, headache, throat irritation, and dizziness. (6)

To report SUSPECTED ADVERSE REACTIONS, contact Liquidia Technologies, Inc. at 1-888-393-LQDA (5732) or FDA at 1-800-FDA-1088 or www.fda.gov/medwatch.

FULL PRESCRIBING INFORMATION

1 INDICATIONS AND USAGE

1.1 Pulmonary Arterial Hypertension

YUTREPIA is indicated for the treatment of pulmonary arterial hypertension (PAH; WHO Group 1) to improve exercise ability. Studies establishing effectiveness predominately included patients with NYHA Functional Class III symptoms and etiologies of idiopathic or heritable PAH (56%) or PAH associated with connective tissue diseases (33%).

The effects diminish over the minimum recommended dosing interval of 4 hours; treatment timing can be adjusted for planned activities.

While there are long-term data on use of treprostinil by other routes of administration, nearly all controlled clinical experience with inhaled treprostinil has been on a background of bosentan (an endothelin receptor antagonist) or sildenafil (a phosphodiesterase type 5 inhibitor). The controlled clinical experience was limited to 12 weeks in duration [see Clinical Studies (14)].

1.2 Pulmonary Hypertension Associated with ILD

YUTREPIA is indicated for the treatment of pulmonary hypertension associated with interstitial lung disease (PH-ILD; WHO Group 3) to improve exercise ability. The study establishing effectiveness predominately included patients with etiologies of idiopathic interstitial pneumonia (IIP) (45%) inclusive of idiopathic pulmonary fibrosis (IPF), combined pulmonary fibrosis and emphysema (CPFE) (25%), and WHO Group 3 connective tissue disease (22%) [see Clinical Studies (14.2)].

2 DOSAGE AND ADMINISTRATION

2.1 Usual Dosage In Adults

YUTREPIA capsules are for oral inhalation only and should be used only with the supplied inhaler. Do not swallow YUTREPIA capsules.

YUTREPIA Dosing in treprostinil-naïve patients:

In patients naïve to treprostinil, therapy should begin with 26.5 mcg 3 to 5 times per day, in 2 breaths based on patient response.

Dosing in patients transitioning from treprostinil inhalation solution (Tyvaso):

Patients transitioning from treprostinil inhalation solution (Tyvaso), can begin YUTREPIA therapy 3 to 5 times per day, in 2 breaths, using the doses specified below (Table 1):

Table 1: YUTREPIA Dosing in Patients Transitioning from Treprostinil Inhalation Solution
Current Tyvaso Dose* | YUTREPIA Dose
(Number of Breaths) | mcg
5 or less breaths | 26.5 mcg
6 to 8 breaths | 53 mcg
9 to 11 breaths | 79.5 mcg
12 to 14 breaths | 106 mcg
15 to 17 breaths | 132.5 mcg
18 or more breaths | 159 mcg
*Each breath of Tyvaso delivers approximately 6 mcg of treprostinil.

In treprostinil-naïve patients and those transitioning from treprostinil inhalation solution, dose increases of 26.5 mcg per dose each week may be implemented, as tolerated. The target maintenance dosage is 79.5 mcg to 106 mcg, 4 times daily.

Doses above 848 mcg per day have not been studied in patients with PAH.

If a scheduled dose is missed, resume therapy as soon as possible at the usual dose.

3 DOSAGE FORMS AND STRENGTHS

YUTREPIA inhalation powder contained in capsule available in 4 strengths:

- 26.5 mcg: opaque yellow cap and clear body capsule with “LIQUIDIA 26.5” in black radial imprint on capsule cap.
- 53 mcg: opaque green cap and clear body capsule with “LIQUIDIA 53” in white radial imprint on capsule cap.
- 79.5 mcg: opaque blue cap and clear body capsule with “LIQUIDIA 79.5” in white radial imprint on capsule cap.
- 106 mcg: opaque purple cap and clear body capsule with “LIQUIDIA 106” in white radial imprint on capsule cap.

4 CONTRAINDICATIONS

None

5 WARNINGS AND PRECAUTIONS

5.1 Risk of Symptomatic Hypotension

Treprostinil is a pulmonary and systemic vasodilator. In patients with low systemic arterial pressure, treatment with treprostinil may produce symptomatic hypotension.

5.2 Risk of Bleeding

Treprostinil inhibits platelet aggregation and increases the risk of bleeding.

5.3 Effect of Other Drugs on Treprostinil

Co-administration of a cytochrome P450 (CYP) 2C8 enzyme inhibitor (e.g., gemfibrozil) may increase exposure (both Cmax and AUC) to treprostinil. Co-administration of a CYP2C8 enzyme inducer (e.g., rifampin) may decrease exposure to treprostinil. Increased exposure is likely to increase adverse events associated with treprostinil administration, whereas decreased exposure is likely to reduce clinical effectiveness [see Drug Interactions (7.1) and Clinical Pharmacology (12.3)].

5.4 Bronchospasm

Like other inhaled prostaglandins, YUTREPIA may cause acute bronchospasm. Patients with asthma or chronic obstructive pulmonary disease (COPD), or other bronchial hyperreactivity, are at increased risk for bronchospasm. Ensure that such patients are treated optimally for reactive airway disease prior to and during treatment with YUTREPIA.

6 ADVERSE REACTIONS

The following potential adverse reactions are described in Warnings and Precautions (5):

- Decrease in systemic blood pressure [see Warnings and Precautions (5.1)].
- Bleeding [see Warnings and Precautions (5.2)].

6.1 Clinical Trials Experience

Because clinical trials are conducted under widely varying conditions, adverse reaction rates observed in the clinical trials of a drug cannot be directly compared to rates in the clinical trials of another drug and may not reflect the rates observed in practice.

The safety and tolerability of YUTREPIA was evaluated in an open label study (INSPIRE) of 121 patients with PAH (WHO Group 1 and NYHA Functional Class II [80 patients] and Class III [41 patients]) followed for up to 2 months. The most commonly reported adverse reactions included cough, headache, throat irritation, dizziness, which are known side effects of treprostinil inhalation solution. Table 2 lists the adverse reactions that occurred at a rate of at least 4% of the overall INSPIRE safety population. The adverse reactions in the INSPIRE study were consistent with those observed in previous studies of inhaled treprostinil.

Table 2: Adverse Reactions Occurring in ≥ 4% of Patients in the INSPIRE Study
Adverse Reaction | Transition* N=55 | Add-On† N=66
Adverse Reaction | n (%) | n (%)
Cough | 15 (27) | 36 (55)
Headache | 14 (25) | 18 (27)
Throat Irritation | 5 (9) | 14 (21)
Dizziness | 6 (11) | 7 (11)
Diarrhea | 3 (6) | 8 (12)
Chest Discomfort | 5 (9) | 5 (8)
Nausea | 4 (7) | 5 (8)
Dyspnea | 3 (6) | 3 (5)
Flushing | 1 (2) | 5 (8)
Oropharyngeal Pain | 1 (2) | 4 (6)
*Transition: Patients were on stable doses of treprostinil inhalation solution for at least 3 months prior to enrollment in the study and transitioned to treatment with YUTREPIA.
†Add-on: Patients were prostacyclin-naïve and were taking no more than 2 approved oral PAH therapies for at least 3 months at time of enrollment and addition of treatment with YUTREPIA.

6.2 Adverse Reactions Identified in Post-Marketing Experience

The following adverse reaction has been identified during the post-approval use of treprostinil inhalation solution. Because this reaction is reported voluntarily from a population of uncertain size, it is not always possible to reliably estimate the frequency or establish a causal relationship to drug exposure:

- Angioedema

7 DRUG INTERACTIONS

7.1 Effect of Cytochrome P450 Inhibitors and Inducers

In vitro studies of human hepatic microsomes showed that treprostinil does not inhibit cytochrome P450 (CYP) isoenzymes CYP1A2, CYP2A6, CYP2C8, CYP2C9, CYP2C19, CYP2D6, CYP2E1 and CYP3A.

Additionally, treprostinil does not induce cytochrome P450 isoenzymes CYP1A2, CYP2B6, CYP2C9, CYP2C19, and CYP3A.

Human pharmacokinetic studies with an oral formulation of treprostinil (treprostinil diolamine) indicated that co-administration of the cytochrome P450 (CYP) 2C8 enzyme inhibitor gemfibrozil increases exposure (both Cmax and AUC) to treprostinil. Co-administration of the CYP2C8 enzyme inducer rifampin decreases exposure to treprostinil. It is unclear if the safety and efficacy of treprostinil by the inhalation route are altered by inhibitors or inducers of CYP2C8 [see Warnings and Precautions (5.3)].

7.2 Effect of Other Drugs on Treprostinil

Drug interaction studies have been carried out with treprostinil (oral or subcutaneous) co-administered with acetaminophen (4 g/day), warfarin (25 mg/day), and fluconazole (200 mg/day), respectively, in healthy volunteers. These studies did not show a clinically significant effect on the pharmacokinetics of treprostinil. Treprostinil does not affect the pharmacokinetics or pharmacodynamics of warfarin. The pharmacokinetics of R- and S- warfarin and the INR in healthy subjects given a single 25 mg dose of warfarin were unaffected by continuous subcutaneous infusion of treprostinil at an infusion rate of 10 ng/kg/min.

8 USE IN SPECIFIC POPULATIONS

8.1 Pregnancy

Risk Summary

Limited case reports of treprostinil use in pregnant women are insufficient to inform a drug-associated risk of adverse developmental outcomes. However, there are risks to the mother and the fetus associated with pulmonary arterial hypertension (see Clinical Considerations). In animal studies, no adverse reproductive and developmental effects were seen for treprostinil at ^39 and ^3145 times the human exposure when based on Cmax and AUC, respectively, following a single YUTREPIA dose of 79.5 mcg [see Clinical Pharmacology (12.3)].

The estimated background risk of major birth defects and miscarriage for the indicated populations is unknown. All pregnancies have a background risk of birth defect, loss, or other adverse outcomes. In the U.S. general population, the estimated background risk of major birth defects and miscarriage in clinically recognized pregnancies is 2 to 4% and 15 to 20%, respectively.

Clinical Considerations

Disease-associated maternal and embryo-fetal risk

Pulmonary arterial hypertension is associated with an increased risk of maternal and fetal mortality.

Data

Animal reproduction studies have been conducted with treprostinil via continuous subcutaneous administration and with treprostinil diolamine administered orally. In studies with orally administered treprostinil diolamine, no adverse effect doses for fetal viability/growth, fetal development (teratogenicity), and postnatal development were determined in rats. In pregnant rats, no evidence of harm to the fetus was observed following oral administration of treprostinil diolamine at the highest dose tested (20 mg/kg/day), which represents about 154 and 1479 times the human exposure, when based on Cmax and AUC, respectively, following a single YUTREPIA dose of 79.5 mcg. In pregnant rabbits, external fetal and soft tissue malformations and fetal skeletal malformation occurred. The dose at which no adverse effects were seen (0.5 mg/kg/day) represents about 9 and 145 times the human exposure, when based on Cmax and AUC, respectively, following a single YUTREPIA dose of 79.5 mcg. No treprostinil treatment-related effects on labor and delivery were seen in animal studies. Animal reproduction studies are not always predictive of human response.

8.2 Lactation

Risk Summary

There are no data on the presence of treprostinil in human milk, the effects on the breastfed infant, or the effects on milk production.

8.4 Pediatric Use

Safety and effectiveness in pediatric patients have not been established.

8.5 Geriatric Use

Placebo-controlled clinical studies of treprostinil inhalation solution did not include sufficient numbers of patients aged 65 years and over to determine whether they respond differently from younger patients. The open-label INSPIRE study in PAH patients included 28 patients aged 65 and over in which no age-related differences were noted. In general, dose selection for an elderly patient should be cautious, reflecting the greater frequency of hepatic, renal, or cardiac dysfunction, and of concomitant diseases or other drug therapy.

8.6 Patients with Hepatic Insufficiency

Plasma clearance of treprostinil, delivered subcutaneously, was reduced up to 80% in subjects with mild-to-moderate hepatic insufficiency. Uptitrate slowly when treating patients with hepatic insufficiency because of the risk of an increase in systemic exposure which may lead to an increase in dose-dependent adverse effects. Treprostinil has not been studied in patients with severe hepatic insufficiency [see Clinical Pharmacology (12.3)].

8.7 Patients with Renal Insufficiency

No dose adjustments are required in patients with renal impairment. Treprostinil is not cleared by dialysis [see Clinical Pharmacology (12.3)].

10 OVERDOSAGE

In general, symptoms of overdose with treprostinil include flushing, headache, hypotension, nausea, vomiting, and diarrhea. Provide general supportive care until the symptoms of overdose have resolved.

11 DESCRIPTION

YUTREPIA contains treprostinil sodium, a prostacyclin mimetic. The chemical name for tresprostinil sodium is 2-{[(1R,2R,3aS,9aS)-2-hydroxy-1-[(3S)-3-hydroxyoctyl]-1H,2H,3H,3aH,4H,9H,9aH-cyclopenta[b]naphthalen-5-yl]oxy}acetic acid, sodium salt with the structural formula:

Treprostinil sodium has a molecular formula of C23H33O5Na and a molecular weight of 412.49 daltons equivalent to 390.5 daltons of Treprostinil.

YUTREPIA inhalation powder contained in a capsule is intended for oral inhalation. The capsule contains white to off-white powder of treprostinil sodium and the inactive ingredients L-leucine, polysorbate 80, sodium chloride, sodium citrate, and trehalose. Each 5 mg of YUTREPIA inhalation powder contains 26.5 mcg of treprostinil, where 26.5 mcg of treprostinil is equivalent to 28 mcg of treprostinil sodium.

The accompanying inhalation device for delivery of YUTREPIA inhalation powder is a disposable plastic device used to inhale the dry powder contained in the HPMC capsule.

The amount of drug delivered to the lungs will vary depending on patient factors such as inspiratory flow and peak inspiratory flow through the inhalation device, which may vary from patient to patient.

Under standardized in vitro testing, the inhalation device delivers the following amounts of treprostinil for each of the YUTREPIA inhalation powder capsule strengths:

YUTREPIA Inhalation Powder Delivered Dose

Capsule Strength (treprostinil) | Dose Delivered a
26.5 mcg | 15.1 mcg
53 mcg | 36.0 mcg
79.5 mcg | 56.6 mcg
106 mcg | 75.7 mcg
a Amount of treprostinil delivered from the device mouthpiece under an in vitro flow rate of 99 L/min with a collection time of 1.2 seconds (2 L total volume).

12 CLINICAL PHARMACOLOGY

12.1 Mechanism of Action

The major pharmacologic actions of treprostinil are direct vasodilation of pulmonary and systemic arterial vascular beds and inhibition of platelet aggregation.

12.2 Pharmacodynamics

In animals, the vasodilatory effects reduce right and left ventricular afterload and increase cardiac output and stroke volume. Other studies have shown that treprostinil causes a dose-related negative inotropic and lusitropic effect. No major effects on cardiac conduction have been observed. Treprostinil produces vasodilation and tachycardia.

Cardiac Electrophysiology

In a clinical trial of 240 healthy volunteers, single doses of treprostinil inhalation solution 54 mcg (the target maintenance dose per session) and 84 mcg (supratherapeutic inhalation dose) prolonged the corrected QTc interval by approximately 10 ms. The QTc effect dissipated rapidly as the concentration of treprostinil decreased.

12.3 Pharmacokinetics

Absorption

In healthy volunteer studies, the systemic exposure (AUC and Cmax) post-inhalation was shown to be proportional to the YUTREPIA doses administered (25 mcg – 150 mcg). The treprostinil mean Cmax, mean AUCinf and median Tmax following a single inhaled target maintenance dose of 79.5 mcg YUTREPIA were 1.48 ng/mL, 1.04 hr.ng/mL and 0.13 hr, respectively.

Distribution

In vitro treprostinil is 91% bound to human plasma proteins over the 330-10,000 ng/mL concentration range.

Metabolism and Excretion

Of subcutaneously administered treprostinil, only 4% is excreted unchanged in urine. Treprostinil is substantially metabolized by the liver, primarily by CYP2C8. Metabolites are excreted in urine (79%) and feces (13%) over 10 days. Five apparently inactive metabolites were detected in the urine, each accounting for 10‑15% of the dose administered. Four of the metabolites are products of oxidation of the 3-hydroxyloctyl side chain and one is a glucuroconjugated derivative (treprostinil glucuronide).

Elimination

Following inhaled administration of YUTREPIA, disposition and elimination is monophasic with a half-life of approximately 30 minutes.

Specific Populations

Hepatic Insufficiency

Plasma clearance of treprostinil, delivered subcutaneously, was reduced up to 80% in subjects presenting with mild-to-moderate hepatic insufficiency. Treprostinil has not been studied in patients with severe hepatic insufficiency [see Use in Specific Populations (8.6)].

Renal Insufficiency

In patients with severe renal impairment requiring dialysis (n=8), administration of a single 1 mg dose of orally administered treprostinil pre-and post-dialysis resulted in AUC0-inf that was not significantly altered compared to healthy subjects [see Use in Specific Populations (8.7)].

13 NONCLINICAL TOXICOLOGY

13.1 Carcinogenesis, Mutagenesis, Impairment of Fertility

Carcinogenesis

A two-year rat carcinogenicity study was performed with treprostinil inhalation solution at target treprostinil doses of 5.26, 10.6, and 34.1 mcg/kg/day. There was no evidence for carcinogenic potential associated with treprostinil inhalation in rats at systemic exposure levels up to 35 times following a single YUTREPIA dose of 79.5 mcg [see Clinical Pharmacology (12.3)]. In vitro and in vivo genetic toxicology studies did not demonstrate any mutagenic or clastogenic effects of treprostinil. Treprostinil sodium did not affect fertility or mating performance of male or female rats given continuous subcutaneous (sc) infusions at rates of up to 450 ng treprostinil/kg/min. In this study, males were dosed from 10 weeks prior to mating and through the 2-week mating period. Females were dosed from 2 weeks prior to mating until gestational day 6.

Oral administration of treprostinil diolamine to Tg.rasH2 mice at 0, 5, 10 and 20 mg/kg/day in males and 0, 3, 7.5 and 15 mg/kg/day in females daily for 26 weeks did not significantly increase the incidence of tumors.

Treprostinil diolamine was tested in vivo in a rat micronucleus assay and did not induce an increased incidence of micronucleated polychromatic erythrocytes.

13.2 Animal Toxicology and/or Pharmacology

In a 2-year rat study with treprostinil inhalation at target doses of 5.26, 10.6, and 34.1 mcg/kg/day, there were more deaths (11) in the mid- and high-dose treprostinil groups during the first 9 weeks of the study, compared to 1 in control groups. At the high-dose level, males showed a higher incidence of inflammation in teeth and preputial gland, and females showed high incidences of inflammation and urothelial hyperplasia in the urinary bladder. The exposures in rats at mid- and high-dose levels were about 15 and 35 times, respectively, the clinical exposure following a single YUTREPIA dose of 79.5 mcg [see Clinical Pharmacology (12.3)].

14 CLINICAL STUDIES

14.1 Pulmonary Arterial Hypertension (WHO Group 1)

TRIUMPH I was a 12-week, randomized, double-blind, placebo-controlled multi-center study of patients with PAH. The study population included 235 clinically stable patients with pulmonary arterial hypertension (WHO Group 1), nearly all with NYHA Class III (98%) symptoms who were receiving either bosentan (an endothelin receptor antagonist) or sildenafil (a phosphodiesterase-5 inhibitor) for at least three months prior to study initiation. Concomitant therapy also could have included anticoagulants, other vasodilators (e.g., calcium channel blockers), diuretics, oxygen, and digitalis, but not a prostacyclin. These patients were administered either placebo or treprostinil inhalation solution in four daily treatment sessions with a target dose of 9 breaths (equivalent to 79.5 mcg YUTREPIA) per session over the course of the 12-week study. Patients were predominantly female (82%), had the origin of PAH as idiopathic/heritable (56%), secondary to connective tissue diseases (33%) or secondary to HIV or previous use of anorexigens (12%); bosentan was the concomitant oral medication in 70% of those enrolled, sildenafil in 30%.

The primary efficacy endpoint of the trial was the change in six-minute walk distance (6MWD) relative to baseline at 12 weeks. 6MWD was measured at peak exposure (between 10 and 60 minutes after dosing), and 3‑5 hours after bosentan or 0.5-2 hours after sildenafil. Patients receiving treprostinil inhalation solution had a placebo-corrected median change from baseline in peak 6MWD of 20 meters at Week 12 (p<0.001).

The distribution of these 6MWD changes from baseline at Week 12 were plotted across the range of observed values (Figure 1). 6MWD measured at trough exposure (defined as measurement of 6MWD at least 4 hours after dosing) improved by 14 meters. There were no placebo-controlled 6MWD assessments made after 12 weeks.

Figure 1. Distributions of 6MWD Changes from Baseline at Week 12 during Peak Plasma Concentration of Treprostinil Inhalation Solution

The placebo-corrected median treatment effect on 6MWD was estimated (using the Hodges-Lehmann estimator) within various subpopulations defined by age quartile, gender, geographic region of the study site, disease etiology, baseline 6MWD quartile, and type of background therapy (Figure 2).

Figure 2. Placebo-Corrected Median Treatment Effect (Hodges-Lehmann estimate with 95% CI) on 6MWD Change from Baseline at Week 12 During Peak Plasma Concentration of Treprostinil Inhalation Solution for Various Subgroups

14.2 Pulmonary Hypertension Associated with ILD (WHO Group 3)

INCREASE was a 16-week, randomized, double-blind, placebo-controlled, multicenter study that enrolled 326 patients with PH-ILD. Enrolled study patients predominately had etiologies of idiopathic interstitial pneumonia (45%) inclusive of idiopathic pulmonary fibrosis, combined pulmonary fibrosis and emphysema (25%), and WHO Group 3 connective tissue disease (22%). The mean baseline 6MWD was 260 meters.

Patients in the INCREASE study were randomized (1:1) to either placebo or treprostinil inhalation solution in four daily treatment sessions with a target dose of 9 breaths (equivalent to 79.5 mcg YUTREPIA) per session and a maximum dose of 12 breaths (equivalent to 106 mcg YUTREPIA) per session over the course of the 16-week study. Approximately 75% of patients randomized to treprostinil inhalation solution titrated up to a dose of 9 breaths, 4 times daily or greater, with 48% of patients randomized to treprostinil inhalation solution reaching a dose of 12 breaths, 4 times daily during the study. The primary efficacy endpoint was the change in 6MWD measured at peak exposure (between 10 and 60 minutes after dosing) from baseline to Week 16. Patients receiving treprostinil inhalation solution had a placebo-corrected median change from baseline in peak 6MWD of 21 meters at Week 16 (p=0.004) using Hodges-Lehmann estimate (Figure 3).

Figure 3: Hodges-Lehmann Estimate of Treatment Effect by Visit for 6MWD at Peak Exposure (PH-ILD)

The treatment effect on 6MWD at Week 16 was consistent for various subgroups, including etiology of PH-ILD, disease severity, age, sex, baseline hemodynamics, and dose (Figure 4).

Figure 4: Forest Plot on Subgroup Analyses of Peak 6MWD (Meter) at Week 16 (PH-ILD)

Time to clinical worsening in the INCREASE study was defined as the time of randomization until 1 of the following criteria were met: hospitalization due to a cardiopulmonary indication, decrease in 6MWD >15% from baseline directly related to PH-ILD at 2 consecutive visits and at least 24 hours apart, death (all causes), or lung transplantation. Treatment with treprostinil inhalation solution in patients with PH-ILD resulted in numerically fewer hospitalizations. The numbers of reported deaths were the same for both treatment groups (Table 3). Overall, treatment with treprostinil inhalation solution demonstrated a statistically significant increase in the time to first clinical worsening event (log-rank test p=0.041; Figure 5), and a 39% overall reduction in the risk of a clinical worsening event (HR=0.61 [95% CI; 0.40, 0.92]; Figure 5).

Table 3: Clinical Worsening Events (PH-ILD)
 |  | Tyvaso n=163 n (%) | Placebo n=163 n (%) | HR (95% CI)
Clinical worsening |  | 37 (22.7%) | 54 (33.1%) | 0.61 (0.40, 0.92)
First contributing event | Hospitalization due to a cardiopulmonary indication | 18 (11.0%) | 24 (14.7%)
First contributing event | Decrease in 6MWD > 15% from baseline directly related to PH-ILD | 13 (8.0%) | 26 (16.0%)
First contributing event | Death (all causes) | 4 (2.5%) | 4 (2.5%)
First contributing event | Lung transplantation | 2 (1.2%) | 0
 |  | Tyvaso n=163 n (%) | Placebo n=163 n (%) | HR (95% CI)
First of each event | Hospitalization due to a cardiopulmonary indication | 21 (12.9) | 30 (18.4%)
First of each event | Decrease in 6MWD > 15% from baseline directly related to PH-ILD | 16 (9.8%) | 31 (19.0%)
First of each event | Death (all causes) | 8 (4.9%) | 10 (6.1%)
First of each event | Lung transplantation | 2 (1.2%) | 1 (0.6%)

Figure 5: Kaplan-Meier Plot of Time to Clinical Worsening Events (PH-ILD)

16 HOW SUPPLIED/STORAGE AND HANDLING

YUTREPIA is supplied in a carton consisting of 1 capsule based, dry powder inhaler (referred to as “inhaler”), 28 capsules (7 foil blister cards of 4 capsules each), and 7 single-use cleaning brushes. The individual capsule well is connected by an air channel to a separate blister well containing a desiccant strip. Descriptions of YUTREPIA carton by capsule strength are provided in Table 4 below:

Table 4: YUTREPIA Carton Contents by Capsule Strength
Capsule Strength (mcg treprostinil) | Capsule Description | NDC Number
26.5 | Opaque yellow cap, clear body, imprinted with “LIQUIDIA 26.5” in black ink radially on cap | 72964-011-01
53 | Opaque green cap, clear body, imprinted with “LIQUIDIA 53” in white ink radially on cap | 72964-012-01
79.5 | Opaque blue cap, clear body, imprinted with “LIQUIDIA 79.5” in white ink radially on cap | 72964-013-01
106 | Opaque purple cap, clear body, imprinted with “LIQUIDIA 106” in white ink radially on cap | 72964-014-01

YUTREPIA inhalation powder capsules should only be delivered using the capsule-based inhaler. The off-white plastic inhaler consists of a blue protective cap marked with YUTREPIA and a base with a mouthpiece, capsule chamber, and two blue push buttons. Discard the inhaler device after 7 days of use or 56 actuations, whichever comes first.

Store at 20°C to 25°C (68°F to 77°F); excursions permitted to 15°C to 30°C (59°F to 86°F) [see USP Controlled Room Temperature].

Capsules should remain in the blister to protect them from moisture and light, and each capsule should be removed only when ready to administer a dose.

Keep out of the reach of children.

17 PATIENT COUNSELING INFORMATION

Advise the patient to read the FDA-approved patient labeling (Instructions for Use).

Train patients in the administration process for YUTREPIA, including dosing, inhaler preparation, administration, cleaning, and maintenance, according to the instructions for use [see Instructions for Use].

To avoid potential interruptions in drug delivery because of equipment malfunction, patients should have access to a back-up.

If a scheduled dose is missed, resume therapy as soon as possible at the usual dose.

©Copyright 2025 Liquidia Technologies, Inc. All rights reserved.

Distributed by: Liquidia Technologies, Inc. Morrisville, NC 27560

Instructions for Use

YUTREPIATM (you-TREP-ee-uh)
(treprostinil)
inhalation powder, for oral inhalation

This Instructions for Use contains information on how to inhale YUTREPIATM. Read these Instructions for Use before you start using YUTREPIA and each time you get a refill. There may be new information. This information does not take the place of talking to your healthcare provider about your medical condition or treatment.

Your healthcare provider should show you or your caregiver how to use YUTREPIA the right way before you use it for the first time.

Important information you need to know before inhaling YUTREPIA inhalation powder:

- Do not swallow YUTREPIA capsules. YUTREPIA is for inhalation only.
- Use YUTREPIA as prescribed by your healthcare provider.
- YUTREPIA capsules come in 4 strengths: 26.5 mcg, 53 mcg, 79.5 mcg, and 106 mcg.
- If your prescribed dose is more than 106 mcg, you will need to inhale 2 YUTREPIA capsules. See Figure C: Dosing Chart to help you identify the 2 capsules needed for your prescribed dose. Only use the capsule combinations in the Dosing Chart when your prescribed dose is more than 106 mcg.
- The capsule must be inhaled within 5 minutes of opening the blister card or the full dose may not be administered. Read through this instruction sheet prior to the first use of this product.
- Always inhale each capsule 2 times to make sure you get your full dose of YUTREPIA.
- Do not wash the inhaler. Keep the inhaler dry.
- Wash and dry your hands before using YUTREPIA.
- If the contents of the capsule comes in contact with your skin or eyes, rinse the area immediately with water.
- YUTREPIA capsules should remain in the blister card(s) and each capsule should be removed only when ready to deliver a dose.

Storing YUTREPIA

- Store YUTREPIA carton in a clean, dry place at room temperature between 68°F to 77°F (20°C to 25°C).
- Leave YUTREPIA capsules in blister card to protect from moisture and light.
- Throw away the inhaler after 7 days of use or 56 capsules whichever comes first.
- Keep YUTREPIA and all medicines out of the reach of children.

Text

Illustration

Get to know YUTREPIA

The YUTREPIA carton contains (See Figure A):

- 1 dry powder inhaler (called “inhaler” in these instructions)
- 7 Foil blister cards of YUTREPIA capsules (called “capsules” in these instructions) containing 4 capsules each, in one of 4 available strengths
- 7 Cleaning brushes (1 for each day)
- 1 Desiccant tab within each blister strip to keep the capsule dry and prevent moisture. Throw away the blister strip and the desiccant tab after removing the capsule.

Preparing to use YUTREPIA

The capsule must be inhaled within 5 minutes of opening the blister card. Ensure all supplies are gathered and you are familiar with the use of the product prior to opening the card.

STEP 1. Gather your supplies.

a. Place your YUTREPIA carton on a clean, dry surface.
b. Remove the inhaler and foil blister cards from the carton (See Figure B).

STEP 2. Select the capsule(s) for your dose.

Use the Dosing Chart (See Figure C) to help you identify the capsule(s) needed for your prescribed dose.

- If your prescribed dose is more than 106 mcg, you will need to inhale 2 capsules per the Dosing Chart (see Figure C).
- Only load and inhale 1 capsule at a time.
- All capsules in a carton are the same strength. If your prescribed dose requires 2 capsules of different strengths, you will need to select your capsules from 2 separate cartons.

IMPORTANT: For doses requiring 2 capsules, only use the capsule combinations presented in the Dosing Chart (See Figure C). The order for inhaling 2 capsules does not matter, regardless of capsule strength.

STEP 3. Check the inhaler and blister card(s).

a. Look at the inhaler and blister card(s) to make sure they are not damaged (See Figure D).
  Do not use the inhaler or capsules if they are damaged.
b. Look at the expiration date on the blister cards to make sure it has not passed (See Figure E).
  Do not use the capsules if the expiration date has passed.

Loading YUTREPIA

STEP 4. Open the inhaler.

a. Pull the cover straight off the inhaler (See Figure F).
b. Rotate the mouthpiece in the direction of the arrow (counter-clockwise) to open the inhaler and expose the capsule chamber (See Figure G).
  If the mouthpiece separates from the base of the inhaler, gently reattach the 2 pieces and continue to follow the instructions.

STEP 5. Remove the capsule from the blister strip.

a. Separate 1 blister strip by tearing at the pre-cut lines (See Figure H).
  Do not remove a capsule from the blister strip until you are ready to deliver your dose.
b. Peel the foil away from the blister strip, remove the capsule (See Figure I).
  Do not swallow the capsule.
  Do not push the capsule through the foil.
  Do not remove the desiccant tab.
  Capsule must be used within 5 minutes of opening the blister card.

STEP 6. Secure the capsule in the inhaler.

a. Hold the inhaler in an upright position.
b. Place the capsule in the capsule chamber in the base of the inhaler (See Figure J). Only load 1 capsule.
  Do not place a capsule in the mouthpiece.
  Do not swallow capsules.

STEP 7. Puncture the capsule.

a. Put one finger on top of the capsule to hold it down (See Figure K).
b. While still holding down the capsule, firmly press both puncture buttons all the way in with your other hand (See Figure L).
  Then let go of (release) the puncture buttons.
  This will puncture the capsule. You only need to press the puncture buttons 1 time.
c. Hold the base of the inhaler and
  rotate the mouthpiece to close it.

Inhaling YUTREPIA

STEP 8. Position the inhaler.

a. Hold the inhaler upright and away from your mouth. (See Figure M).
  Do not hold the inhaler by the puncture buttons.

STEP 9. Breathe out (exhale).

a. Breathe out fully and away from the inhaler (See Figure N).
  Do not exhale into the mouthpiece.

STEP 10. Breathe in deeply (inhale)

a. Close your lips around the mouthpiece (See Figure O).
b. Tilt your head back slightly (See Figure O).
c. Take a comfortable deep breath in (inhale) until your lungs feel full (See Figure O).
  As you inhale, you will hear or feel a whirring noise as the capsule spins and releases medicine.

STEP 11. Hold breath, then breathe out (exhale).

a. Take the inhaler out of your mouth and hold your breath for 5 seconds or as long as you comfortably can (See Figure P).
b. Then breathe out normally.

IMPORTANT: If you cough when inhaling, repeat STEP 8 through11.

STEP 12. Inhale again.

a. To make sure the capsule is completely emptied of medicine, repeat STEP 8 through11 (See Figure Q).
  Always inhale each capsule 2 times to make sure you get your full dose.

Removing and disposing of the capsule

STEP 13. Open the inhaler.

a. Rotate the mouthpiece in the direction of the arrow (counter-clockwise) to open the inhaler and expose the capsule chamber (See Figure R).
b. Remove the used (empty) capsule and throw away (dispose of) into household trash (See Figure S).
c. See box below if you need to use more than 1 capsule to complete your prescribed dose.
d. Continue to Step 14 if you have completed your prescribed dose.

Closing and storing the inhaler

STEP 14. Close the inhaler.

a. Hold the base of the inhaler and rotate the mouthpiece to close it (See Figure T).
b. Put the cover on the inhaler (See Figure U).
c. Store the inhaler in a clean, dry place at room temperature.

Cleaning the inhaler (at end of each day)

Clean the outside and inside of the inhaler after your last dose of the day.

a. Wipe the mouthpiece with a dry paper towel, tissue, or clean dry cloth (See Figure V).
b. Use the cleaning brush provided to clean the capsule chamber in order to remove visible powder buildup (See Figure W).
  NOTE: Throw away the brush after cleaning. Use only 1 brush each day.

Disposing of the inhaler

Throw away (dispose of) the inhaler into household trash after 7 days of use.

a. The inhaler is reusable and will last for 7 days (1 week) or 56 capsules, whichever comes first.
  (See Figure X).

©Copyright 2025 Liquidia Technologies, Inc. All rights reserved.
Distributed by: Liquidia Technologies, Inc. Morrisville, NC 27560
For more information call 1-888-393-LQDA (5732) or go to www.YUTREPIA.com

This Instructions for Use has been approved by the U.S. Food and Drug Administration

Issued: June 2025

PRINCIPAL DISPLAY PANEL – 26.5 mcg Carton

26.5 mcg Carton

NDC 72964-011-01
Rx Only

26.5 mcg
per capsule

Yutrepia™
(treprostinil) inhalation powder

For oral inhalation only
DO NOT SWALLOW YUTREPIA CAPSULES

Contents:

- 28 Capsules (7 Foil blister cards of 4 capsules each)
- 1 Dry powder inhaler
- 7 Single-use cleaning brushes
- Instructions for Use

Liquidia™

NDC 72964-011-01
Rx Only

26.5 mcg
per capsule

Yutrepia™
(treprostinil)
inhalation powder

Read Instructions for Use before each use.
Recommended Dosage: See prescribing information.
Do not remove capsules from blister cards until immediately before use.
Store at 68°F to 77°F (20°C to 25°C); excursions permitted to 59°F to
86°F (15°C to 30°C) [see USP Controlled Room Temperature].
Keep this and all drugs out of the reach of children.

Distributed by:
Liquidia Technologies Inc.
Morrisville, NC 27560

Liquidia™

PRINCIPAL DISPLAY PANEL – 53 mcg Carton

53 mcg Carton

NDC 72964-012-01
Rx Only

53 mcg
per capsule

Yutrepia™
(treprostinil) inhalation powder

For oral inhalation only
DO NOT SWALLOW YUTREPIA CAPSULES

Contents:

- 28 Capsules (7 Foil blister cards of 4 capsules each)
- 1 Dry powder inhaler
- 7 Single-use cleaning brushes
- Instructions for Use

Liquidia™

NDC 72964-012-01
Rx Only

53 mcg
per capsule

Yutrepia™
(treprostinil)
inhalation powder

Read Instructions for Use before each use.
Recommended Dosage: See prescribing information.
Do not remove capsules from blister cards until immediately before use.
Store at 68°F to 77°F (20°C to 25°C); excursions permitted to 59°F to
86°F (15°C to 30°C) [see USP Controlled Room Temperature].
Keep this and all drugs out of the reach of children.

Distributed by:
Liquidia Technologies Inc.
Morrisville, NC 27560

Liquidia™

PRINCIPAL DISPLAY PANEL – 79.5 mcg Carton

79.5 mcg Carton

NDC 72964-013-01
Rx Only

79.5 mcg
per capsule

Yutrepia™
(treprostinil) inhalation powder

For oral inhalation only
DO NOT SWALLOW YUTREPIA CAPSULES

Contents:

- 28 Capsules (7 Foil blister cards of 4 capsules each)
- 1 Dry powder inhaler
- 7 Single-use cleaning brushes
- Instructions for Use

Liquidia™

NDC 72964-013-01
Rx Only

79.5 mcg
per capsule

Yutrepia™
(treprostinil)
inhalation powder

Read Instructions for Use before each use.
Recommended Dosage: See prescribing information.
Do not remove capsules from blister cards until immediately before use.
Store at 68°F to 77°F (20°C to 25°C); excursions permitted to 59°F to
86°F (15°C to 30°C) [see USP Controlled Room Temperature].
Keep this and all drugs out of the reach of children.

Distributed by:
Liquidia Technologies Inc.
Morrisville, NC 27560

Liquidia™

PRINCIPAL DISPLAY PANEL – 106 mcg Carton

106 mcg Carton

NDC 72964-014-01
Rx Only

106 mcg
per capsule

Yutrepia™
(treprostinil) inhalation powder

For oral inhalation only
DO NOT SWALLOW YUTREPIA CAPSULES

Contents:

- 28 Capsules (7 Foil blister cards of 4 capsules each)
- 1 Dry powder inhaler
- 7 Single-use cleaning brushes
- Instructions for Use

Liquidia™

NDC 72964-014-01
Rx Only

106 mcg
per capsule

Yutrepia™
(treprostinil)
inhalation powder

Read Instructions for Use before each use.
Recommended Dosage: See prescribing information.
Do not remove capsules from blister cards until immediately before use.
Store at 68°F to 77°F (20°C to 25°C); excursions permitted to 59°F to
86°F (15°C to 30°C) [see USP Controlled Room Temperature].
Keep this and all drugs out of the reach of children.

Distributed by:
Liquidia Technologies Inc.
Morrisville, NC 27560

Liquidia™